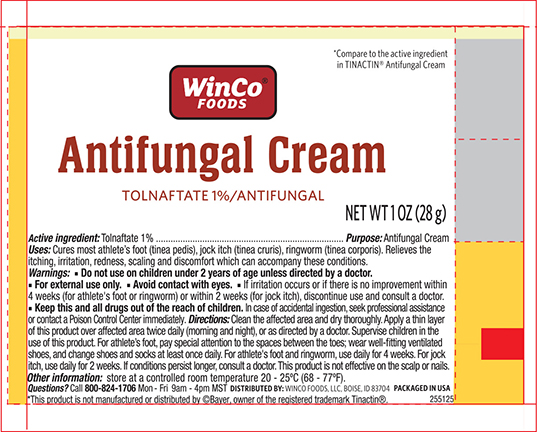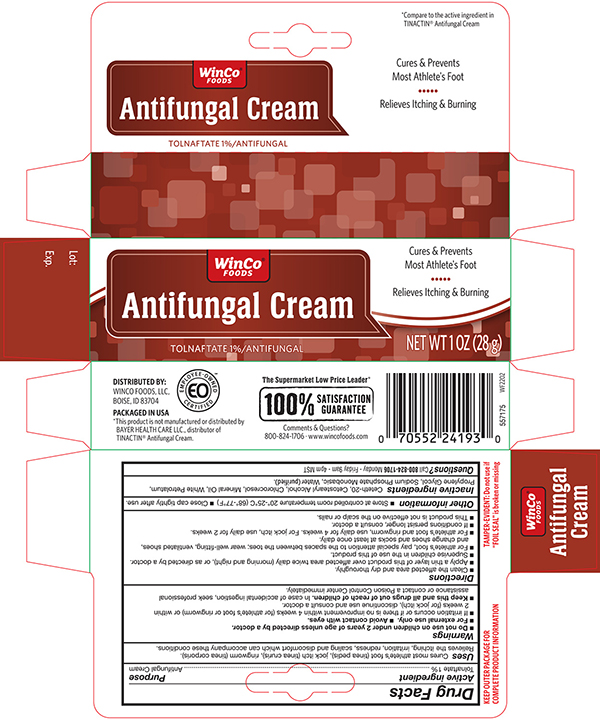 DRUG LABEL: WINCO ANTIFUNGAL
NDC: 67091-051 | Form: CREAM
Manufacturer: WinCo Foods LLC
Category: otc | Type: HUMAN OTC DRUG LABEL
Date: 20241121

ACTIVE INGREDIENTS: TOLNAFTATE 10 mg/1 g
INACTIVE INGREDIENTS: CETETH-20; CETOSTEARYL ALCOHOL; CHLOROCRESOL; MINERAL OIL; PETROLATUM; PROPYLENE GLYCOL; SODIUM PHOSPHATE, MONOBASIC; WATER

Active

Tolnaftate 1%

Purpose

Antifungal

Uses

- Cures most athlete's foot (tinea pedis), jock itch (tinea cruris) and ringworm (tinea corporis).
- Relieves the itching, irratation, redness, scaling and discomfort which can accompany these conditions.

Warnings

- Do not use on children under 2 years of age unless directed by a doctor.
- For external use only avoid contact with eyes.
- Irritation occurs or if there is no improvement within 4 weeks (for athlete's foot and ringworm)irritation occurs or if there is no improvement within 2 weeks (for jock itch).

KEEP OUT OF REACH OF CHILDREN

Keep this and all drugs out of the reach of children.

In case of accidental ingestion, seek professional assistance or contact a Poison Control Center immediately.

Directions

- Clean the affected area and dry thoroughly.
- Apply a thin layer of the product over the affected area twice daily (morning and night) or as directed by a doctor.
- Supervise children in the use of this product.

For athlete's foot

- Pay special attention to the spaces between the toes.
- Wear well fitting ventilated shoes.
- Change shoes and socks at least once daily.
- For athlete's foot and ringworm, use daily for 4 weeks.
- For jock itch, use daily for 2 weeks.
- If condition persists longer, consult a doctor.
- This product is not effective on the scalp or nails.

Other Information

- Store at controlled room temperature 15°-30°C (59°-86°F).
- Close cap tighty after ever use.

Inactives

Ceteth-20, Cetostearyl Alcohol, Chlorocresol, Mineral Oil, White Petrolatum, Propylene Glycol, Sodium Phosphate Monobasic, Water

Questions ?

1-800-222-1087

Principal Display panel -Carton

WINCO NDC 67091-051-28

Antifungal Cream (Tolnaftate 1%)

CURES Most:

ATHLETE'S

FOOTJOCK ITCH

RINGWORM

NET WT. 1.0 OZ (28 g)

Principal Display Panel -Tube

WINCO NDC 67091-051-28

Antifungal Cream (Tolnaftate 1%)

CURES Most:

ATHLETE'S

FOOTJOCK ITCH

RINGWORM

NET WT. 1.0 OZ (28 g)